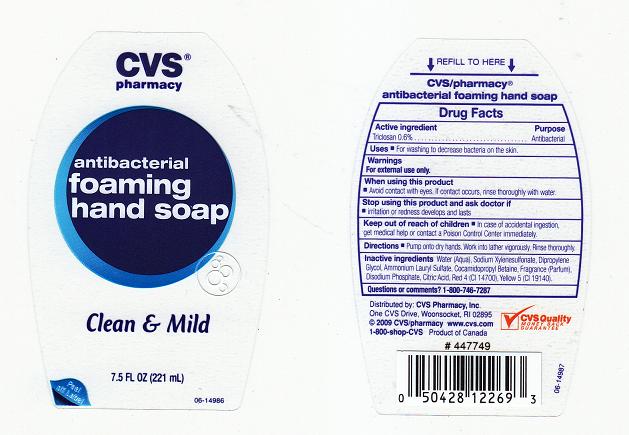 DRUG LABEL: ANTIBACTERIAL FOAMING HAND SP
NDC: 59779-169 | Form: LIQUID
Manufacturer: CVS PHARMACY
Category: otc | Type: HUMAN OTC DRUG LABEL
Date: 20110203

ACTIVE INGREDIENTS: TRICLOSAN 0.6 mL/100 mL
INACTIVE INGREDIENTS: WATER; SODIUM 2,5-DIMETHYLBENZENE-1-SULFONATE; DIPROPYLENE GLYCOL; AMMONIUM LAURYL SULFATE; COCAMIDOPROPYL BETAINE; SODIUM PHOSPHATE, DIBASIC, DIHYDRATE; ANHYDROUS CITRIC ACID; FD&C RED NO. 4; FD&C YELLOW NO. 5

DRUG FACTS

ACTIVE INGREDIENT

TRICLOSAN 0.6%

PURPOSE

ANTIBACTERIAL

USES

FOR WASHING TO DECREASE BACTERIA ON THE SKIN.

WARNINGS

FOR EXTERNAL USE ONLY.

WHEN USING THIS PRODUCT

AVOID CONTACT WITH EYES. IF CONTACT OCCURS, RINSE THROUGHLY WITH WATER.

STOP USING THIS PRODUCT AND ASK DOCTOR IF

IRRITATION OR REDNESS DEVELOPS AND LASTS.

KEEP OUT OF REACH OF CHILDREN

IN CASE OF ACCIDENTAL INGESTION, GET MEDICAL HELP OR CONTACT A POISON CONTROL CENTER IMMEDIATELY.

DIRECTIONS

PUMP ONTO DRY HANDS. WORK INTO LATHER VIGOROUSLY. RINSE THOROUGHLY.

INACTIVE INGREDIENTS

WATER, SODIUM XYLENESULFONATE, DIPROPYLENE GLYCOL, AMMONIUM LAURYL SULFATE, COCAMIDOPROPYL BETAINE, FRAGRANCE,DISODIUM PHOSPHATE, CITRIC ACID, RED 4 (CI 14700),YELLOW 5 (CI 19140).

QUESTIONS OR COMMENTS

1-800-748-7287